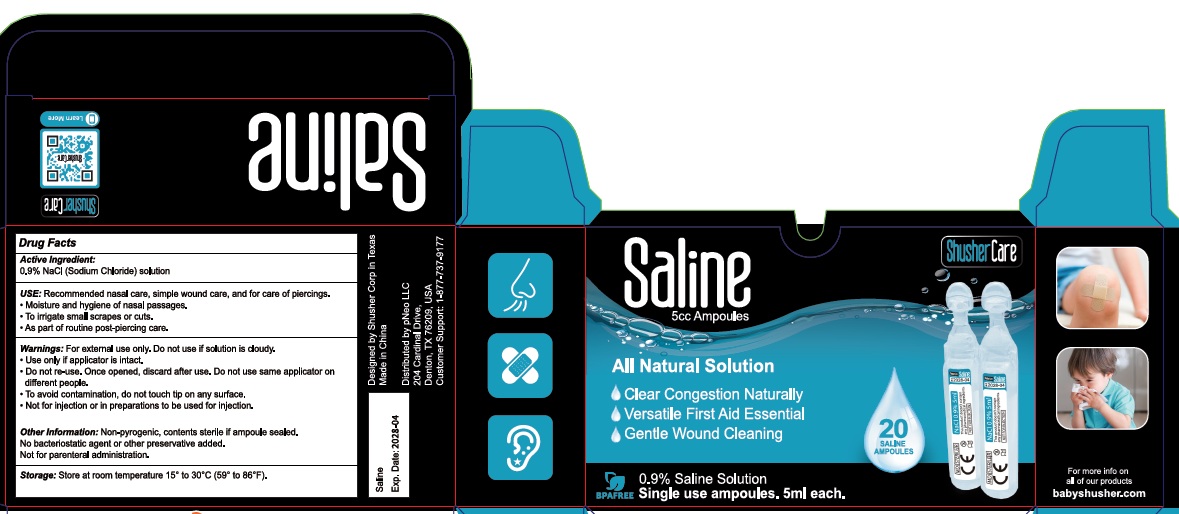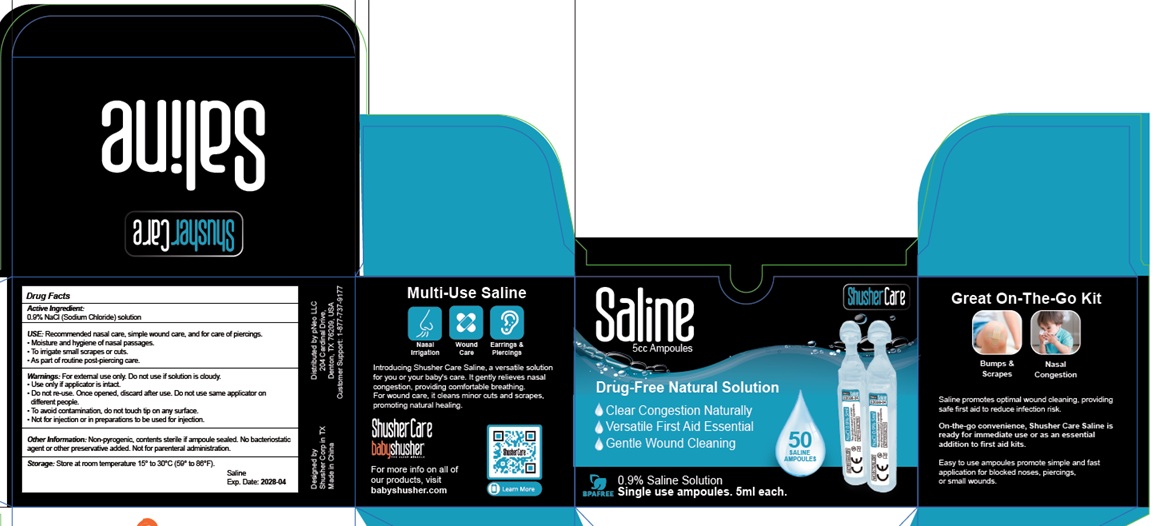 DRUG LABEL: Shusher Care
NDC: 85471-001 | Form: LIQUID
Manufacturer: pNeo LLC
Category: otc | Type: HUMAN OTC DRUG LABEL
Date: 20250401

ACTIVE INGREDIENTS: ISOTONIC SODIUM CHLORIDE SOLUTION 0.9 g/100 mL
INACTIVE INGREDIENTS: WATER

Active Ingredient

0.9% NaCl (sodium chloride) solution

Uses

Recommended nasal care, simple wound care, and for care of piercings

- Moisture and hygiene of nasal passages
- To irrigate small scrapes or cuts
- As part of routine post-piercing care.

Warning

- For external use only. Do not use if solution is cloudy.
- Use only if applicator is intact
- Do not re-use. once opened, discard after use. Do not use same applicator on different people.
- To avoid contamination, do not touch tip on any surface
- Not for injection or in preparation to be used for injection.

Other Information

Non-pyrogenic, contents sterile if ampoule sealed. No bacteriostatic agent or other preservative added. Not for parenteral administration.

Store at room temperature 15° to 30°C (59° to 86°F).